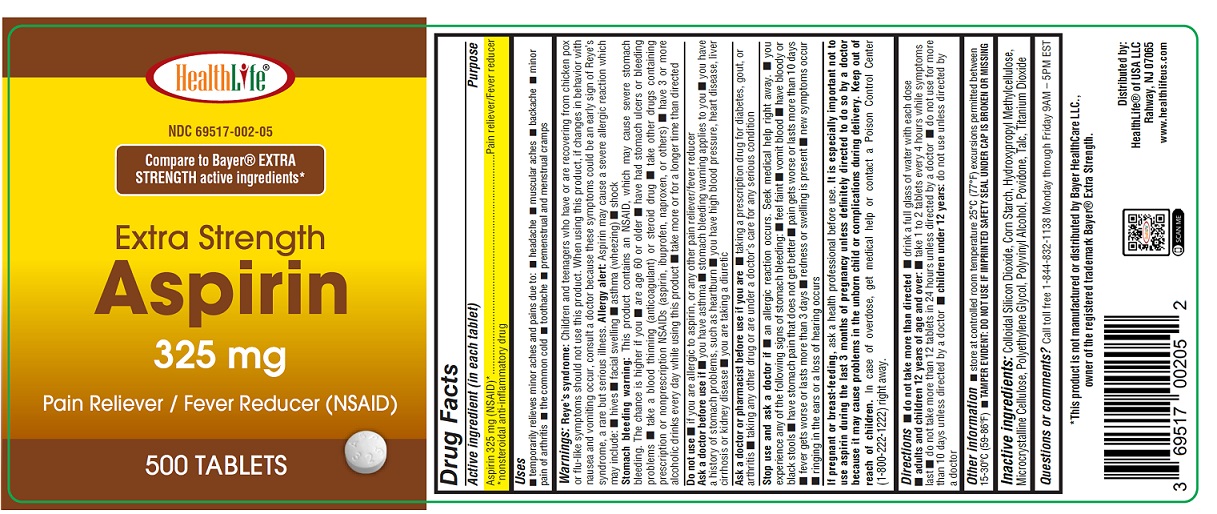 DRUG LABEL: Extra Strength Aspirin 325 mg
NDC: 69517-002 | Form: TABLET, FILM COATED
Manufacturer: HealthLife of USA LLC
Category: otc | Type: HUMAN OTC DRUG LABEL
Date: 20250912

ACTIVE INGREDIENTS: ASPIRIN 325 mg/1 1
INACTIVE INGREDIENTS: SILICON DIOXIDE; STARCH, CORN; HYPROMELLOSE, UNSPECIFIED; MICROCRYSTALLINE CELLULOSE; POLYETHYLENE GLYCOL, UNSPECIFIED; POLYVINYL ALCOHOL; POVIDONE; TALC; TITANIUM DIOXIDE

Active ingredient (in each tablet)

Aspirin 325 mg (NSAID)*

*nonsteroidal anti-inflammatory drug

Purpose

Pain reliever/Fever reducer

Uses

temporary relieves minor aches and pains due to:

- headache
- muscular aches
- backache
- minor pain of arthritis
- the common cold
- toothache
- premenstrual and menstrual cramps

Warnings

Reye’s syndrome: Children and teenagers who have or are recovering from chicken pox or flu-like symptoms should not use this product. When using this product, if changes in behavior with nausea and vomiting occur, consult a doctor because these symptoms could be an early sign of Reye's syndrome, a rare but serious illness.

Allergy alert: Aspirin may cause a severe allergic reaction, which may include:

- hives
- facial swelling
- asthma (wheezing)
- shock

Stomach bleeding warning: This product contains an NSAID, which may cause severe stomach bleeding. The chance is higher if you

- are age 60 or older
- have had stomach ulcers or bleeding problems
- take a blood thinning (anticoagulant) or steroid drug
- take other drugs containing prescription or nonprescription NSAIDs (aspirin, ibuprofen, naproxen, or others)
- have 3 or more alcoholic drinks every day while using this product
- take more or for a longer time than directed

Do not use

- if you are allergic to aspirin or any other pain reliever/fever reducer

Ask a doctor before use if

- you have asthma
- stomach bleeding warning applies to you
- you have a history of stomach problems, such as heartburn
- you have high blood pressure, heart disease, liver cirrhosis, or kidney disease
- you are taking a diuretic

Ask a doctor or pharmacist before use if you are

- taking a prescription drug for diabetes, gout, or arthritis
- taking any other drug or are under a doctor's care for any serious condition

Stop use and ask a doctor if

If

- an allergic reaction occurs. Seek medical help right away.
- you experience any of the following signs of stomach bleeding:
  - feel faint
  - vomit blood
  - have bloody or black stools
  - have stomach pain that does not get better
- pain gets worse or lasts for more than 10 days
- fever gets worse or lasts more than 3 days
- redness or swelling is present
- new symptoms occur
- ringing in the ears or a loss of hearing occurs

If pregnant or breast-feeding,

ask a health professional before use. It is especially important not to use aspirin during the last 3 months of pregnancy unless definitely directed to do so by a doctor because it may cause problems in the unborn child or complications during delivery.

Keep out of reach of children.

In case of overdose, get medical help or contact a Poison Control Center (1-800-222-1222) right away.

Directions

- do not take more than directed
- drink a full glass of water with each dose
- adults and children 12 years of age and over:
  • take 1 to 2 tablets every 4 hours while symptoms last
  • do not take more than 12 tablets in 24 hours unless directed by a doctor
  • do not use for more than 10 days unless directed by a doctor
- children under 12 years:do not use unless directed by a doctor

Other information

- store at controlled room temperature 25ºC (77ºF) execursion permitted between 15-30ºC (59-86ºF)
- TEMPER EVIDENT: DO NOT USE IF IMPRINTED SAFETY SEAL UNDER CAP IS BROKEN OR MISSING

Inactive ingredients

Colloidal Silicon Dioxide, Corn Starch, Hydroxypropyl Methylcellulose, Microcrystalline Cellulose, Polyethylene Glycol, Polyvinyl Alcohol, Povidone, Talc, Titanium Dioxide

Questions or comments?

Call toll free 1 844-832-1138

Monday through Friday 9AM - 5PM EST